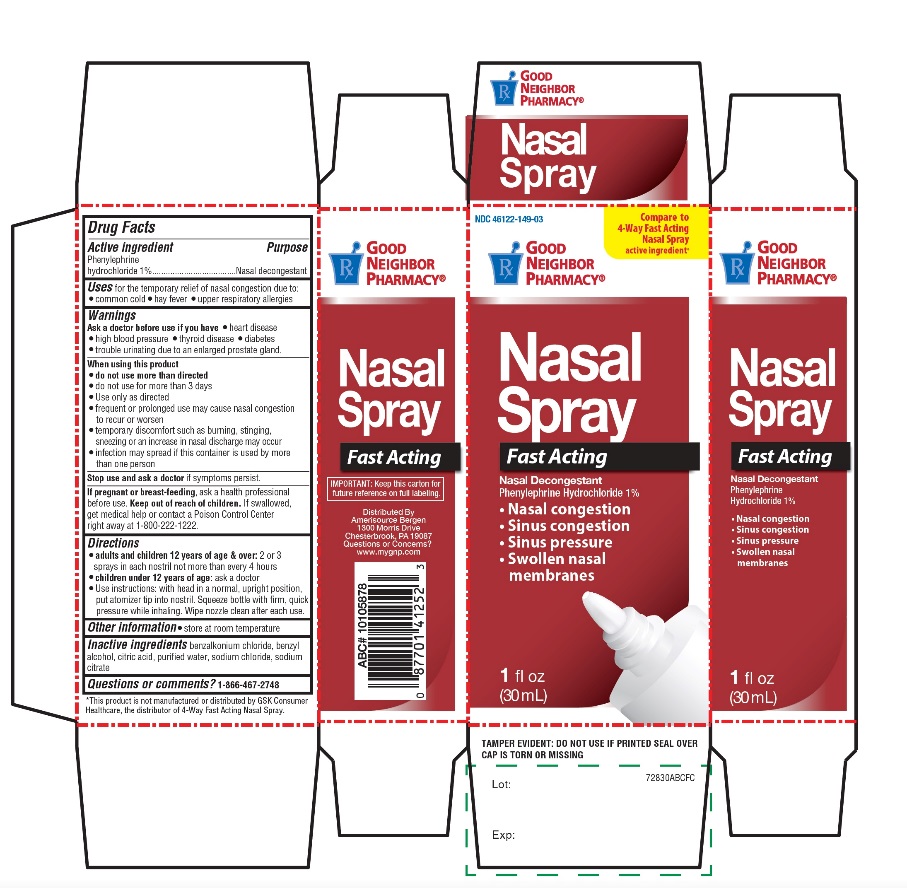 DRUG LABEL: Good Neighbor Pharmacy Fast Acting Nasal
NDC: 46122-149 | Form: SPRAY
Manufacturer: Amerisource Bergen
Category: otc | Type: HUMAN OTC DRUG LABEL
Date: 20250710

ACTIVE INGREDIENTS: PHENYLEPHRINE HYDROCHLORIDE 10 mg/1 mL
INACTIVE INGREDIENTS: BENZALKONIUM CHLORIDE; BENZYL ALCOHOL; CITRIC ACID MONOHYDRATE; WATER; SODIUM CHLORIDE; SODIUM CITRATE, UNSPECIFIED FORM

Good Neighbor Pharmacy Nasal Spray Fast Acting

Active ingredient

Phenylephrine hydrochloride 1%

Purpose

Nasal decongestant

Uses

for the temporarily relief of nasal congestion due to:

- common cold
- hay fever
- upper respiratory allergies

Ask a doctor before use if you have

- heart disease
- high blood pressure
- thyroid disease
- diabetes
- trouble urinating due to an enlarged prostate gland.

When using this product

- do not exceed recommended dosage
- do not use more than 3 days.
- Use only as directed.
- frequent or prolonged use may cause nasal congestion to recur or worsen
- temporary discomfort such as burning, stinging, sneezing, or an increase in nasal discharge may occur
- the use of this container by more than one person may spread infection
- Infection may spread if this container is used by more than one person

Stop use and ask a doctor

if symptoms persist.

If pregnant or breast-feeding

ask a health professional before use.

Keep out of reach of children

If swallowed, get medical help or contact a Poison Control Center right away at 1-800-222-1222

Directions

- adults and children 12 years of age and older: 2 or 3 sprays in each nostril not more than every 4 hours
- children under 12 years of age:ask a doctor
- Use instructions: with head in a normal, upright position, put atomizer tip into nostril. Squeeze bottle with firm, quick pressure while inhaling. Wipe nozzle clean after each use.

Other information

- store at room temperature

Questions or comments?

1-866-467-2748

Inactive ingredients

benzalkonium chloride, benzyl alcohol, citric acid, purified water, sodium chloride, sodium citrate

Principal Display

NDC 46122-149-03

Compare to 4-way® Nasal Spray active ingredient*

GOOD NEIGHBOR PHARMACY®

Nasal Spray

Fast Acting

Nasal Decongestant

Phenylephrine Hydrochloride 1%

- Nasal congestion
- Sinus congestion
- Sinus pressure
- Swollen nasal membranes

1 fl oz (30mL)

TAMPER EVIDENT: DO NOT USE IF PRINTED SEAL OVER CAP IS TORN OR MISSING

*This product is not manufactured or distributed by GSK Consumer Healthcare, the distributor of 4-way® Fast Acting Nasal Spray.

IMPORTANT: Keep this carton for future reference on full labeling.

Distributed By

Amerisource Bergen

1300 Morris Drive

Chesterbrook, PA 19087

Questions or concerns?

www.mygnp.com